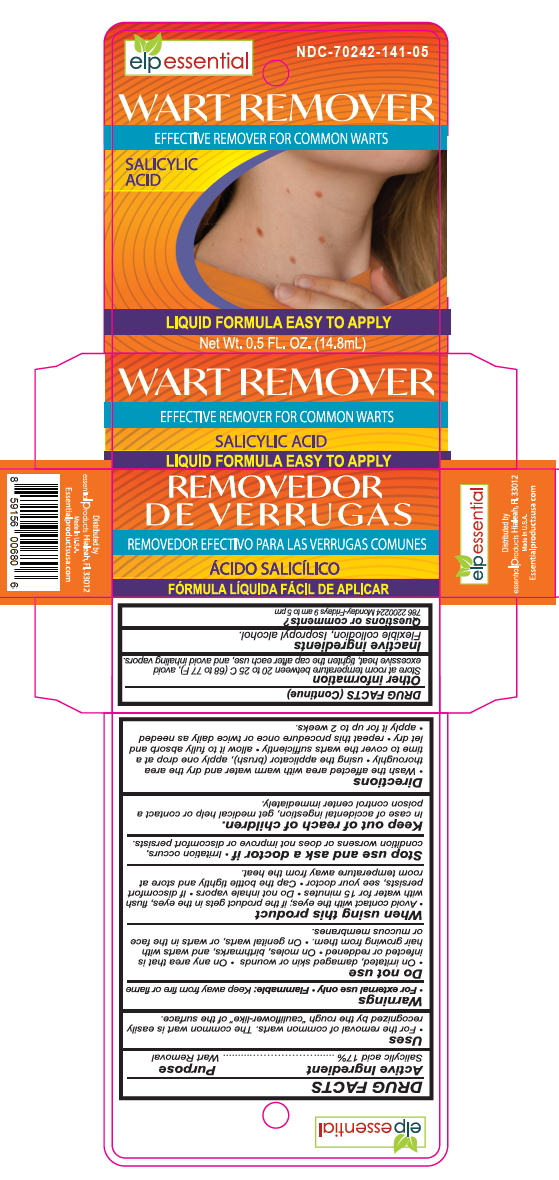 DRUG LABEL: Wart Remover
NDC: 70242-141 | Form: LIQUID
Manufacturer: Dannso Corp./d.b.a. Essential Products
Category: otc | Type: HUMAN OTC DRUG LABEL
Date: 20241106

ACTIVE INGREDIENTS: SALICYLIC ACID 17 mg/100 mL
INACTIVE INGREDIENTS: ISOPROPYL ALCOHOL; CAMPHOR (NATURAL); CASTOR OIL; ETHER; PYROXYLIN; ALCOHOL

Wart Remover

Active Ingredient(s)

Salicylic Acid 17%

Purpose

Wart remover

Use

for the removal of common warts
the common war is easily recognized by the rough macauli flower-like " of the surface

Warnings

For external use

Do not use

On irritated skin or wounds, on any area that is infected or reddened , on moles skin tags , birthmarks , or warts with hair growing from them , genital warts , or warts on the face or mucous membranes

WHEN USING

Avoid contact with the eyes; If product gets in the eyes , flush with water for 15 minutes

Do not inhale vapors

if discomfort persists, see your doctor. Cap the bottle tightly and store at room temperature away from heat.

STOP USE

Irritation occurs, condition worsens or does not improve or discomfort persists

Keep out of reach of children

If product gets into eyes , flush with water for 15 minutes
In case of accidental ingestion , get medical help or contact a Poison Control Center inmediatly

Directions

Wash the affected area with warm water and dry the area thoroughly. Using applicator (brush),

Apply one drop at a time to cover the wart sufficiently

Allow to fully absorb and let dry

Repeat this procedure once or twice daily as needed for up to 2 weeks

Other information

Store at room temperature between 20 and 25 C (68 to 77 F)

Avoid excessive heat, tighten the cap after each use and avoid inhaling vapors.

Inactive ingredients

Flexible Collodion, Isopropyl Alcohol